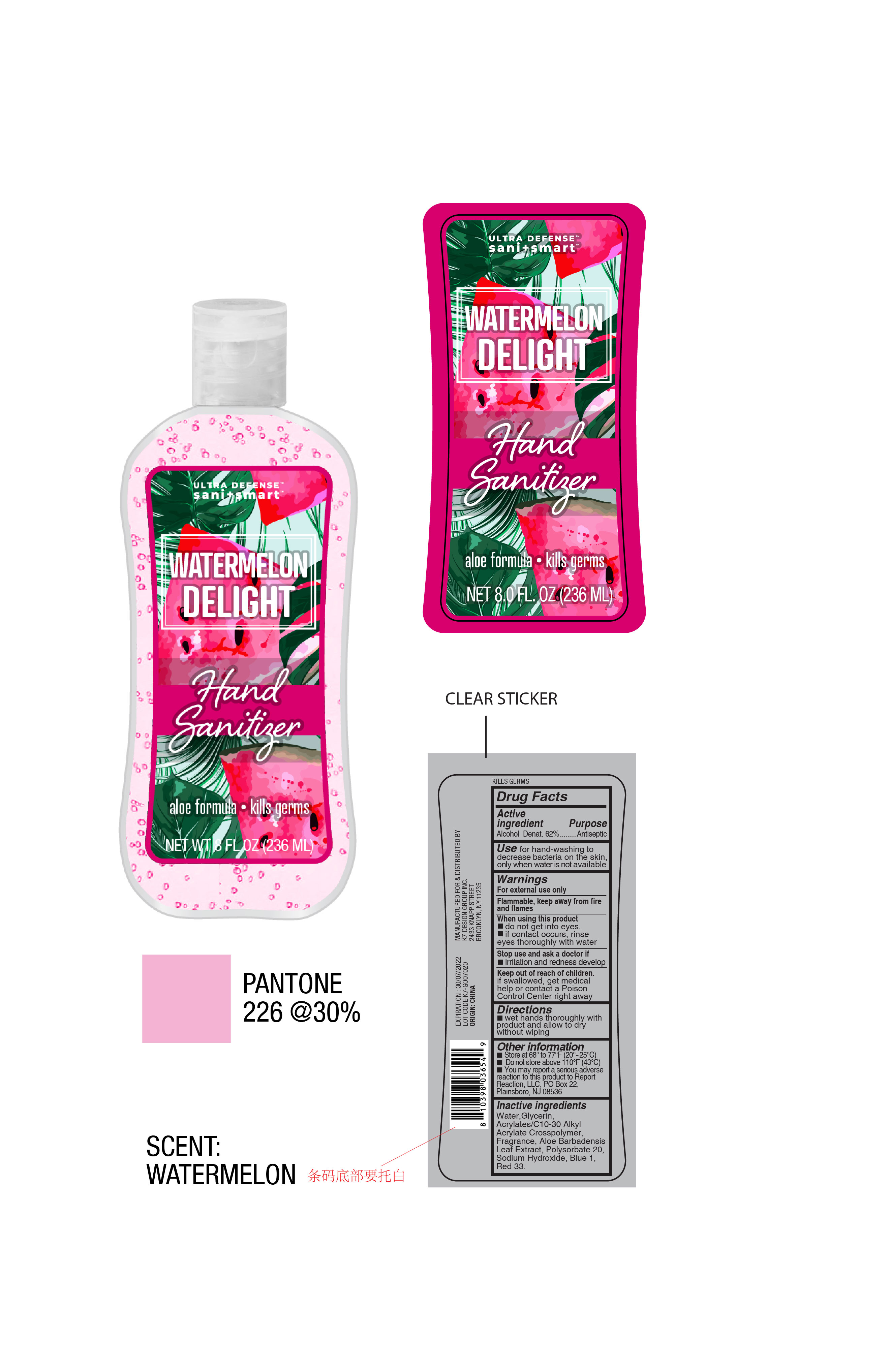 DRUG LABEL: Ultra Defense Sani Smart Watermelon Delight
NDC: 51522-062 | Form: GEL
Manufacturer: Gold Orient International Limited
Category: otc | Type: HUMAN OTC DRUG LABEL
Date: 20200806

ACTIVE INGREDIENTS: ALCOHOL 62 mL/100 mL
INACTIVE INGREDIENTS: GLYCERIN; FD&C BLUE NO. 1; POLYSORBATE 20; SODIUM HYDROXIDE; CARBOMER COPOLYMER TYPE A (ALLYL PENTAERYTHRITOL CROSSLINKED); WATER; D&C RED NO. 33

Ultra Defense Sani Smart Watermelon Delight

Active Ingredient

Alcohol Denat. 62%

Purpose

Antiseptic

Use

for hand-washing to decrease bacteria on the skin, only when water is not available

Warnings

For external use only
Flammable, keep away from fire and flames

When using this product

do not get into eyes.
if contact occurs, rinse eyes thoroughly with water

Stop use and ask a doctor if

irritation and redness develop

Keep out of reach of children

if swallowed, get medical help or contact a Poison Control Center right away

Directions

wet hands thoroughly with product and allow to dry without wiping

Other information

Store at 68° to 77°F (20°~25°C)
Do not store above 110°F (43°C)
You may report a serious adverse reaction to this product to Report Reaction, LLC, PO Box 22, Plainsboro, NJ 08536

Inactive ingredients

Water, Glycerin, Acrylates/C10-30 Alkyl Acrylate Crosspolymer, Fragrance, Aloe Barbadensis Leaf Extract, Polysorbate 20, Sodium Hydroxide, Blue 1, Red 33.